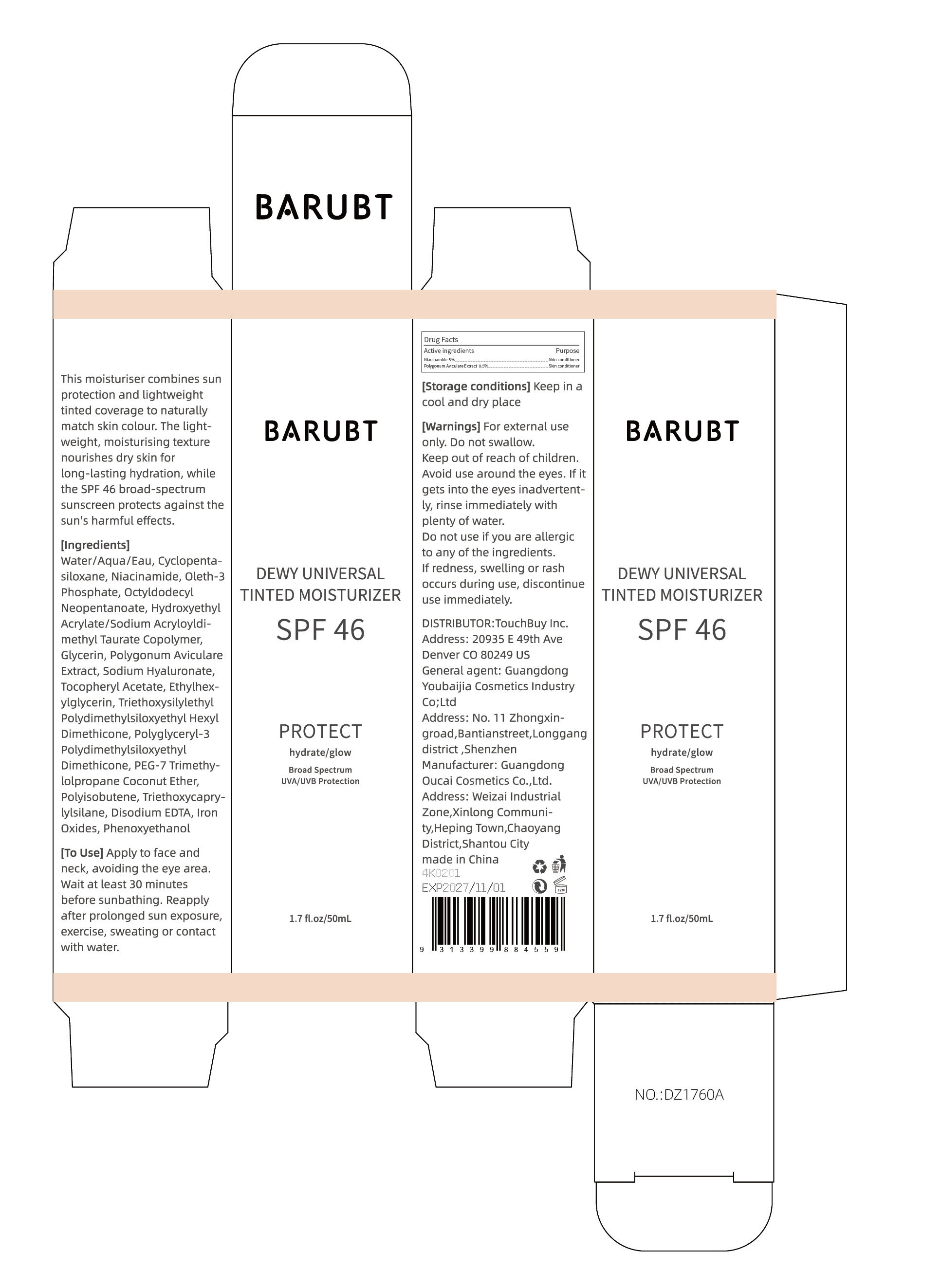 DRUG LABEL: BARUBT DEWY UNIVERSAL TINTED MOISTURIZER
NDC: 84712-038 | Form: CREAM
Manufacturer: Guangdong Youbaijia Cosmetic Industry Co., Ltd
Category: otc | Type: HUMAN OTC DRUG LABEL
Date: 20241128

ACTIVE INGREDIENTS: POLYGONUM AVICULARE WHOLE 0.25 g/50 mL; NIACINAMIDE 2.5 g/50 mL
INACTIVE INGREDIENTS: CYCLOPENTASILOXANE 4 g/50 mL

ACTIVE INGREDIENT

Polygonum Aviculare Extract 0.5%
Niacinamide 5%

INACTIVE INGREDIENT

Water/Aqua/Eau, Cyclopentasiloxane, Oleth-3 Phosphate, Octyldodecyl Neopentanoate, Hydroxyethyl Acrylate/Sodium Acryloyldimethyl Taurate Copolymer, Glycerin, Sodium Hyaluronate, Tocopheryl Acetate, Ethylhexylglycerin, Triethoxysilylethyl Polydimethylsiloxyethyl Hexyl Dimethicone, Polyglyceryl-3 Polydimethylsiloxyethyl Dimethicone, PEG-7 Trimethylolpropane Coconut Ether, Polyisobutene, Triethoxycaprylylsilane, Disodium EDTA, Iron Oxides, Phenoxyethanol

Do not use on damaged or broken skin

Keep away from children. Do not swallow.

PURPOSE

moisturising and sunscreen

QUESTIONS

Contact name: Jessie Peng
Company phone number: +1 818 579 7288
Company e-mail: jessie@registeragentllc.com

STOP USE

lf skin becomes red or irritated, discontinue use immediately and wash with water.

WHEN USING

keep out of eyes. Rinse with water to remove.

WARNINGS

For external use only.

INDICATIONS AND USAGE

This moisturiser combines sun protection and lightweight tinted coverage to naturally match skin colour. The lightweight, moisturising texture nourishes dry skin for long-lasting hydration, while the SPF 46 broad-spectrum sunscreen protects against the sun's harmful effects.

DOSAGE AND ADMINISTRATION

Apply to face and neck, avoiding the eye area.Wait at least 30 minutes before sunbathing. Reapply after prolonged sun exposure, exercise, sweating or contactwith water.